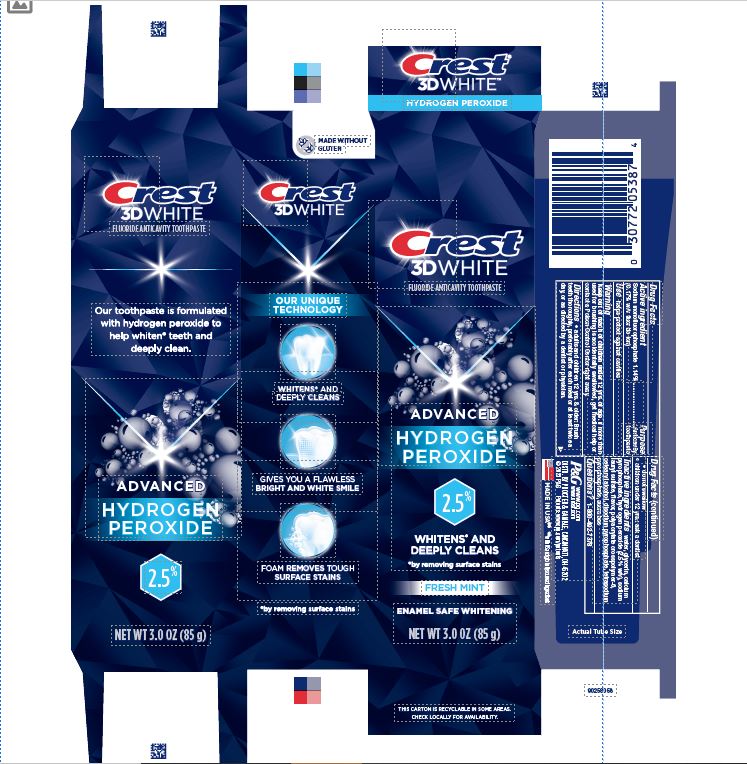 DRUG LABEL: Crest 3D White Advanced
NDC: 69423-752 | Form: PASTE, DENTIFRICE
Manufacturer: The Procter & Gamble Manufacturing Company
Category: otc | Type: HUMAN OTC DRUG LABEL
Date: 20260108

ACTIVE INGREDIENTS: SODIUM MONOFLUOROPHOSPHATE 1.7 mg/1 g
INACTIVE INGREDIENTS: HYDROGEN PEROXIDE; CALCIUM PYROPHOSPHATE; GLYCERIN; SODIUM LAURYL SULFATE; WATER; SUCRALOSE; AMMONIUM ACRYLOYLDIMETHYLTAURATE, DIMETHYLACRYLAMIDE, LAURYL METHACRYLATE AND LAURETH-4 METHACRYLATE COPOLYMER, TRIMETHYLOLPROPANE TRIACRYLATE CROSSLINKED (45000 MPA.S); CETOSTEARYL ALCOHOL; SODIUM ACID PYROPHOSPHATE

Crest 3D White Advanced 2.5% Hydrogen Peroxide

Drug Facts

Sodium monofluorophosphate 1.14%

(0.17% w/v fluoride ion)

Purpose

Anticavity toothpaste

Use

helps protect against cavities

Warning

Keep out of reach of children under 12 yrs. of age. If more than used for brushing is accidentally swallowed, get medical help or contact a Poison Control Center right away.

Directions

- adults and children 12 yrs. & older: Brush teeth thoroughly, preferably after each meal or at least twice a day, or as directed by a dentist or physician.
- do not swallow
- children under 12 yrs.: ask a dentist

Inactive ingredients

water, glycerin, calcium pyrophosphate, hydrogen peroxide (2.5% w/v), sodium lauryl sulfate, ﬂavor, polyacrylate crosspolymer-6, cetearyl alcohol, disodium pyrophosphate, tetrasodium pyrophosphate, sucralose

Questions?

1-800-492-7378

DISTR. BY PROCTER & GAMBLE, CINCINNATI, OH 45202

Crest 3D White Ultra White 85g tube in carton

Crest

3D WHITE

FLUORIDE ANTICAVITY TOOTHPASTE

ADVANCED HYDROGEN PEROXIDE

2.5%

WHITENS* AND DEEPLY CLEANS

*BY REMOVING SURFACE STAINS

FRESH MINT

ENAMEL SAFE WHITENING

NET WT 3.0 OZ (85 g)